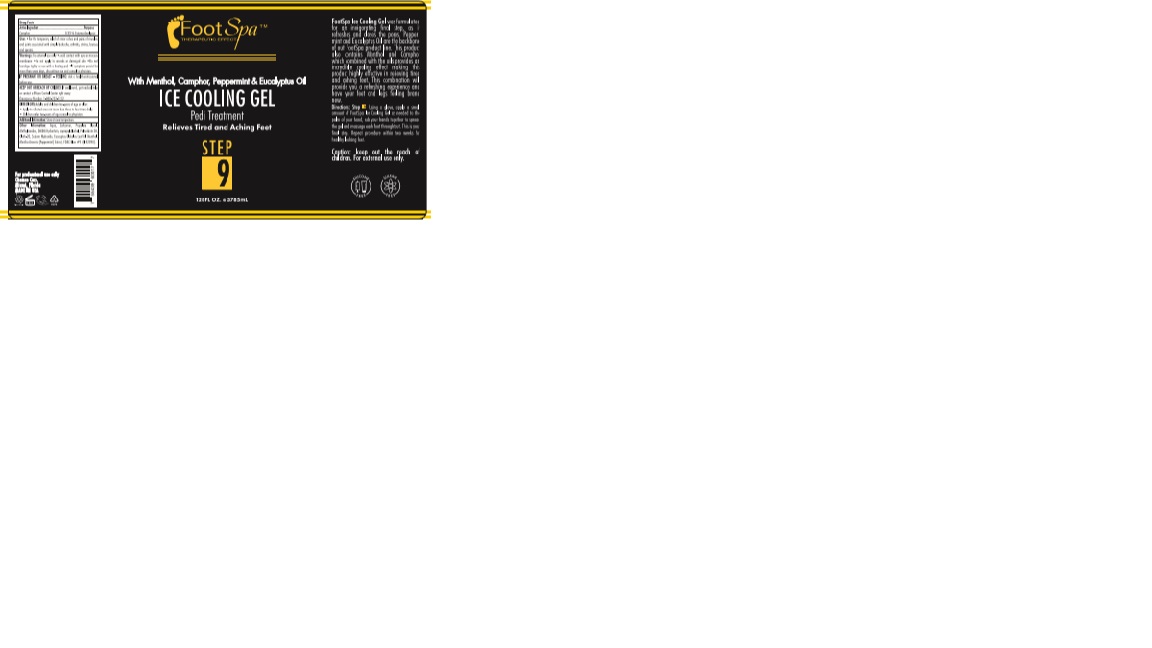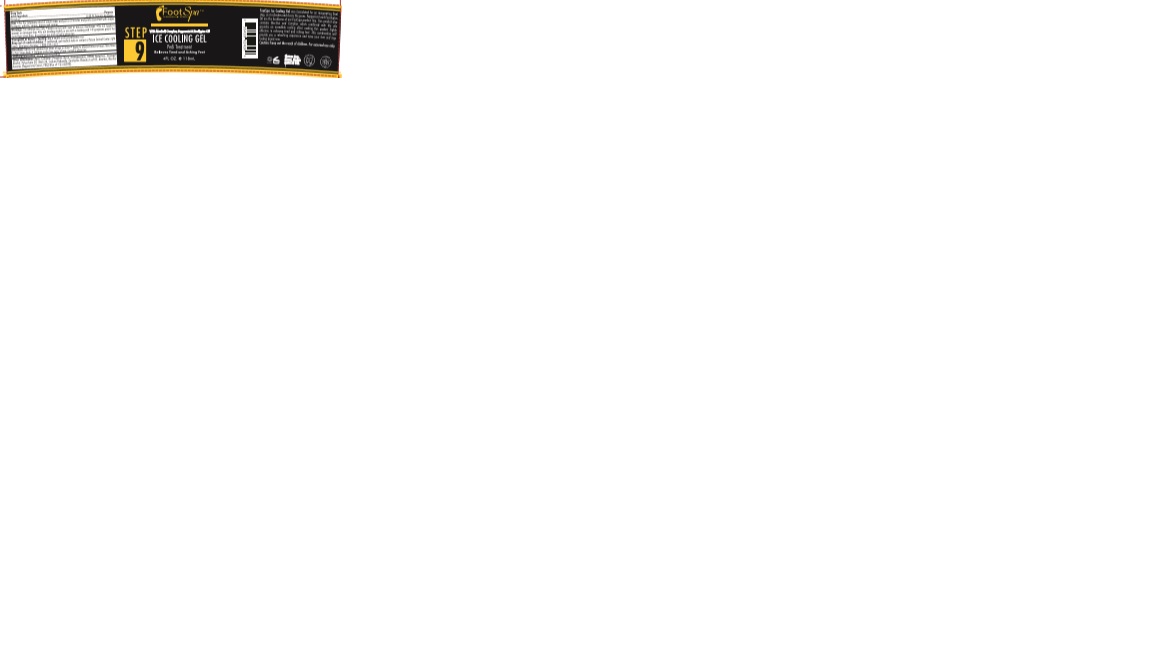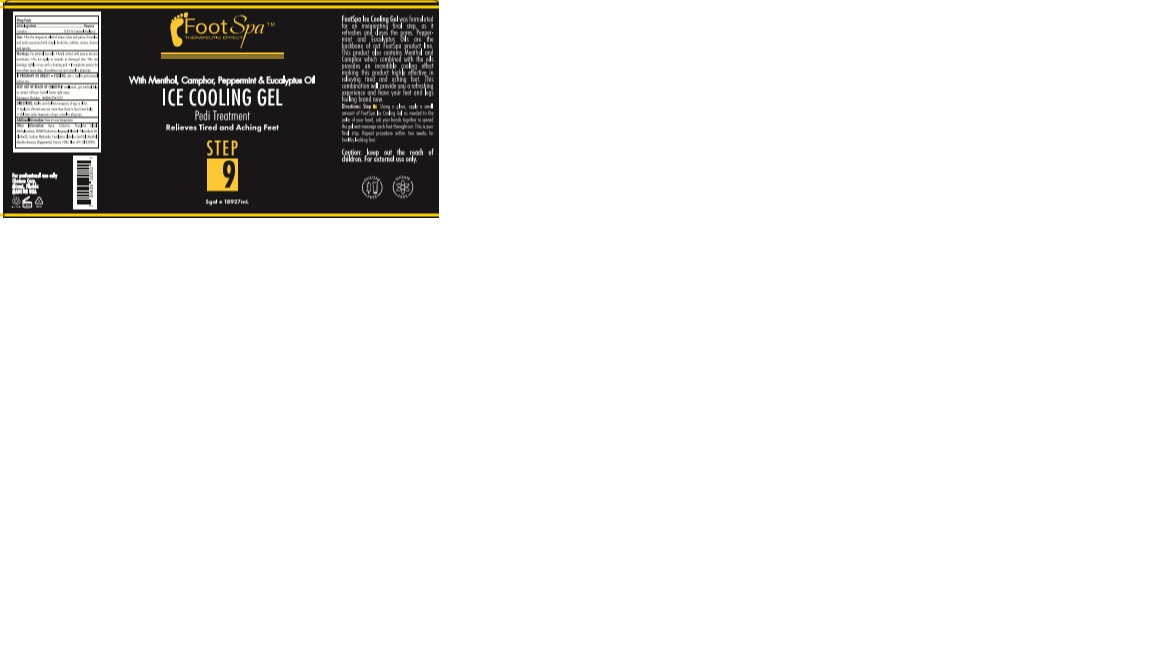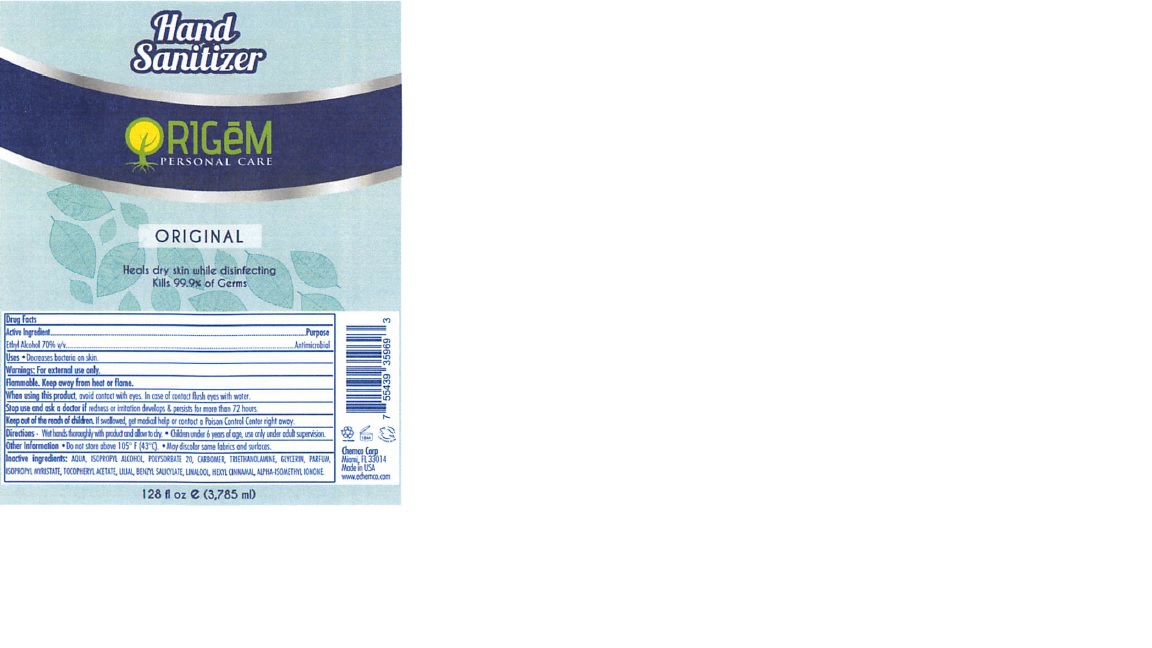 DRUG LABEL: Camphor
NDC: 49283-331 | Form: GEL
Manufacturer: Chemco Corporation
Category: otc | Type: HUMAN OTC DRUG LABEL
Date: 20200623

ACTIVE INGREDIENTS: ISOPROPYL ALCOHOL 94.8 mL/99 mL
INACTIVE INGREDIENTS: EUCALYPTUS GLOBULUS LEAF; WATER; MENTHA ARVENSIS LEAF OIL; POLYSORBATE 20; OLETH-20; MENTHOL; CARBOMER 940; FD&C BLUE NO. 1; DIPROPYLENE GLYCOL MONOCAPRATE MONOCAPRYLATE; METHYLPARABEN; DMDM HYDANTOIN; SODIUM HYDROXIDE

49283-331-04